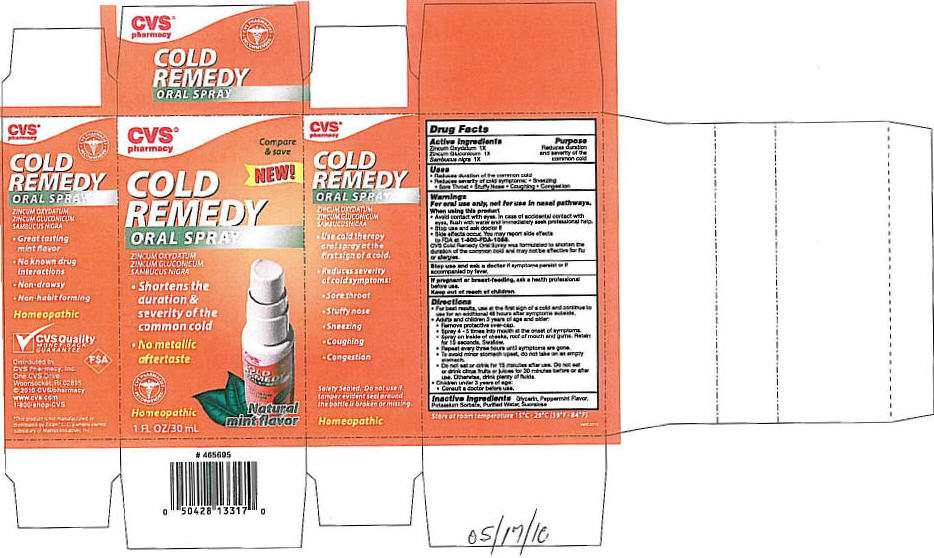 DRUG LABEL: NBB
NDC: 64762-862 | Form: SPRAY, METERED
Manufacturer: Dynamic Pharmaceuticals Inc.
Category: otc | Type: HUMAN OTC DRUG LABEL
Date: 20100524

ACTIVE INGREDIENTS: ZINC OXIDE 0.25 mg/1 mL; ZINC GLUCONATE 12.42 mg/1 mL; SAMBUCUS NIGRA FLOWERING TOP 0.05 mg/1 mL

COLD
REMEDY
ORAL SPRAY

Drug Facts

ACTIVE INGREDIENT

Active Ingredients | Purpose
Zincum Oxydatum 1X | Reduces duration
Zincum Gluconicum 1X | and severity of the
Sambucus nigra 1X | common cold

Uses

- Reduces duration of the common cold
- Reduces severity of cold symptoms:
  - Sneezing
  - Sore Throat
  - Stuffy Nose
  - Coughing
  - Congestion

Warnings

For oral use only, not for use in nasal pathways.

When using this product

- Avoid contact with eyes. In case of accidental contact with eyes, flush with water and immediately seek professional help.
- Stop use and ask doctor if
- Side effects occur. You may report side effects to FDA at 1-800-FDA-1088.

CVS Cold Remedy Oral Spray was formulated to shorten the duration of the common cold and may not be effective for flu or allergies.

Stop use and ask a doctor if symptoms persist or if accompanied by fever.

PREGNANCY OR BREAST FEEDING

If pregnant or breast-feeding, ask a health professional before use.

Keep out of reach of children.

Directions

- For best results, use at the first sign of a cold and continue to use for an additional 48 hours after symptoms subside.
- Adults and children 3 years of age and older:
  - Remove protective over-cap.
  - Spray 4 - 5 times into mouth at the onset of symptoms.
  - Spray on inside of cheeks, roof of mouth and gums. Retain for 15 seconds. Swallow.
  - Repeat every three hours until symptoms are gone.
  - To avoid minor stomach upset, do not take on an empty stomach.
  - Do not eat or drink for 15 minutes after use. Do not eat or drink citrus fruits or juices for 30 minutes before or after use. Otherwise, drink plenty of fluids.
- Children under 3 years of age:
  - Consult a doctor before use.

Inactive Ingredients

Glycerin, Peppermint Flavor, Potassium Sorbate, Purified Water, Sucralose

STORAGE AND HANDLING

Store at room temperature 15°C-29°C (59°F-84°F)

Distributed by:
CVS Pharmacy, Inc.
One CVS Drive
Woonsocket, RI 02895

PRINCIPAL DISPLAY PANEL - 30 mL Bottle Carton

CVS®
pharmacy

Compare
& save

NEW!

COLD
REMEDY
ORAL SPRAY

ZINCUM OXYDATUM
ZINCUM GLUCONICUM
SAMBUCUS NIGRA

- Shortens the
  duration &
  severity of the
  common cold
- No metallic
  aftertaste

CVS PHARMACIST
RECOMMENDED

Homeopathic

Natural
mint flavor

1 FL OZ/30 mL